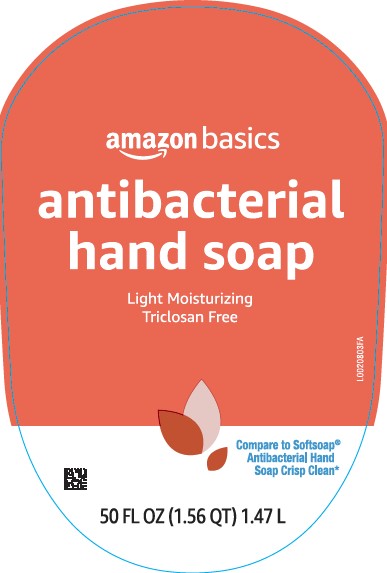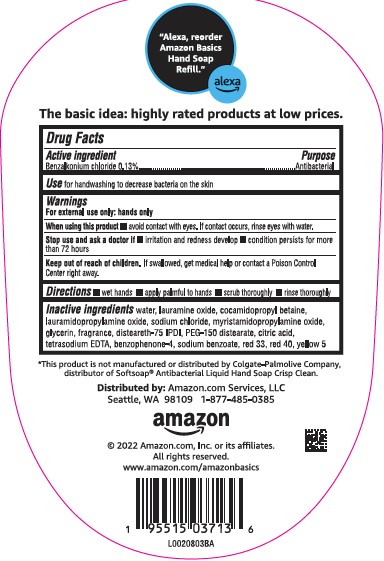 DRUG LABEL: Moisturizing Antibacterial
NDC: 72288-009 | Form: SOAP
Manufacturer: Amazon.com Services LLC
Category: otc | Type: HUMAN OTC DRUG LABEL
Date: 20250702

ACTIVE INGREDIENTS: BENZALKONIUM CHLORIDE 1.3 mg/1 mL
INACTIVE INGREDIENTS: WATER; LAURAMINE OXIDE; COCAMIDOPROPYL BETAINE; LAURAMIDOPROPYLAMINE OXIDE; SODIUM CHLORIDE; MYRISTAMIDOPROPYLAMINE OXIDE; GLYCERIN; DISTEARETH-75 ISOPHORONE DIISOCYANATE; PEG-150 DISTEARATE; CITRIC ACID MONOHYDRATE; EDETATE SODIUM; SULISOBENZONE; SODIUM BENZOATE; D&C RED NO. 33; FD&C RED NO. 40; FD&C YELLOW NO. 5

Basics 279.003/279AD-AE
Light Moisturizing Antibacterial Hand Soap

claims

"Alexa, reorder Amazon Basics Hand Soap Refill." alexa

The baisic idea: highly rated products at low prices.

Active Ingredient

Benzalkonium chlroide 0.13%

Purpose

Antibacterial

Use

for handwashing to decrease bacteria on the skin

Warnings

For external use only: hand only

When using this product

avoid contact with eyes. If contact occurs, rinse eyes thoroughly with water.

Stop use and ask a doctor if

- irritation and redness develop
- condition persists for more than 72 hours

Keep out of reach of children.

If swallowed, get medical help or contact a Poison Control Center right away.

Directions

- wet hands
- apply palmful to hands
- scrub thoroughly
- rinse thoroughly

Inactive ingredients

water, lauramine oxide, cocamidopropyl betaine, lauramidopropylamine oxide, sodium chloride, myristamidopropylamine oxide, glycerin, fragrance, disteareth-75 IPDI, PEG-150 distearate, citric acid, tetrasodium EDTA, benzophenone-4, sodium benzoate, red 33, red 40, yellow 5

Disclaimer

*This product is not manufactured or distributed by Colgate-Palmolive Company, distributor of SoftsoapAntibacterial Liquid Hand Soap Crisp Clean.

ADVERSE REACTION

Distributed by: Amazon.com Services, LLC

Seattle, WA 98109 1-877-485-0385

amazon

2022 Amazon.com, Inc. or its affiliates.

All rights reserved.

www.amazon.com/amazonbasics

principal display panel

amazon basics

antibacterial

hand soap

Light Moisturizing

Triclosan Free

Compare to Softsoap®Antibacterial Hand Soap Crisp Clean*

50 FL OZ (1.56 QT) 1.47 L